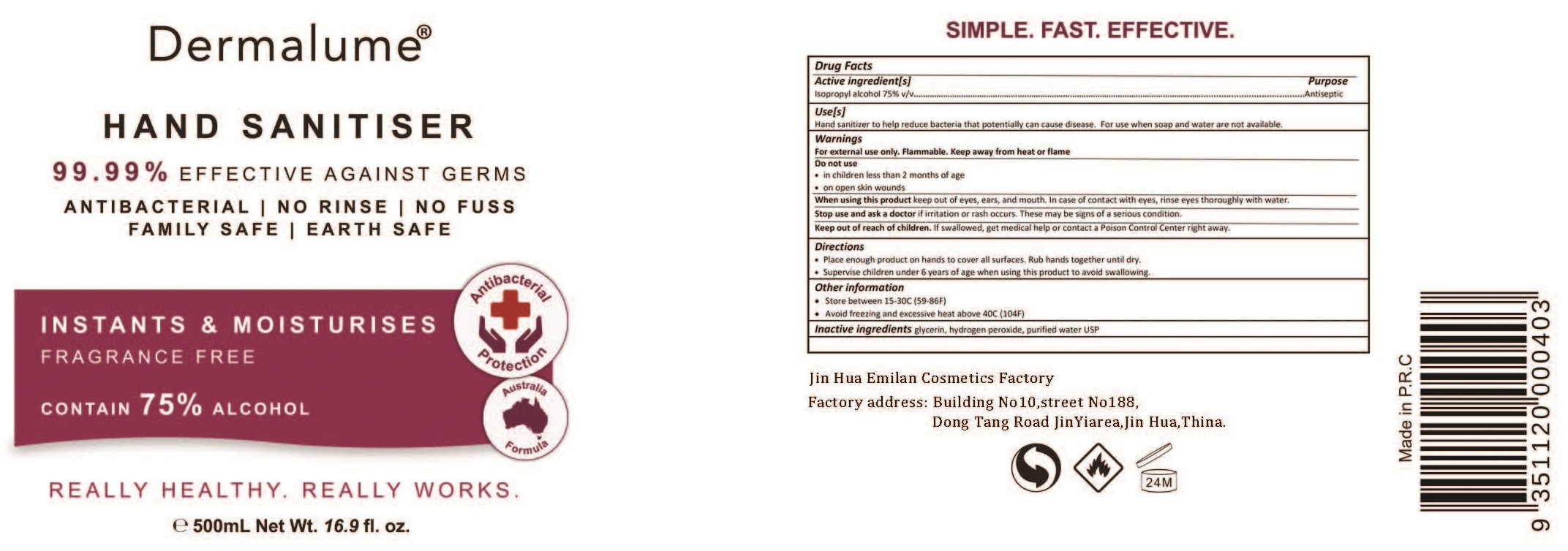 DRUG LABEL: HAND SANITISER
NDC: 54665-002 | Form: LIQUID
Manufacturer: Jinhua Emilan Cosmetics Factory
Category: otc | Type: HUMAN OTC DRUG LABEL
Date: 20200629

ACTIVE INGREDIENTS: ISOPROPYL ALCOHOL 375 mL/500 mL
INACTIVE INGREDIENTS: GLYCERIN; WATER; HYDROGEN PEROXIDE

DOSAGE AND ADMINISTRATION

●Store between 15-30°C (59-86°F)
●Avoid freezing and excessive heat above 40°C (104°F)

INACTIVE INGREDIENT

Glycerin，hydrogen peroxide，purified water USP

INDICATIONS AND USAGE

1.Place enough product on hands to cover all surfaces. Rub hands together until dry.
2.Supervise children under 6 vears of age when using this product to avoid swallowing.

ACTIVE INGREDIENT

isopropyl alcohol

keep out of reach of children

PURPOSE

Disinfection
Sterilization
No Rinseing

WARNINGS

For external use only. Flammable. Keep away from heat or flame